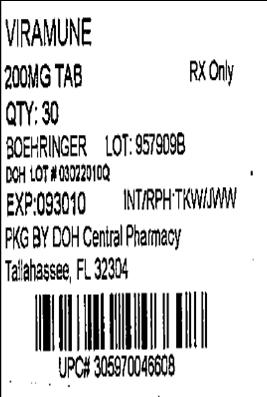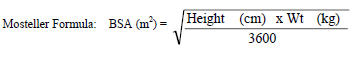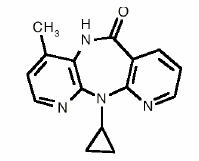 DRUG LABEL: Viramune
NDC: 53808-0808 | Form: TABLET
Manufacturer: State of Florida DOH Central Pharmacy
Category: prescription | Type: HUMAN PRESCRIPTION DRUG LABEL
Date: 20100521

ACTIVE INGREDIENTS: NEVIRAPINE 200 mg/1 1
INACTIVE INGREDIENTS: CELLULOSE, MICROCRYSTALLINE ; LACTOSE MONOHYDRATE; POVIDONE; SODIUM STARCH GLYCOLATE TYPE A POTATO; SILICON DIOXIDE; MAGNESIUM STEARATE

HIGHLIGHTS OF PRESCRIBING INFORMATION

These highlights do not include all the information needed to use VIRAMUNE safely and effectively. See full prescribing information for VIRAMUNE.
Viramune® (nevirapine) tablets 200 mg
Viramune® (nevirapine) oral suspension 50 mg/5 mL
Initial U.S. Approval: 1996

WARNING: LIFE-THREATENING (INCLUDING FATAL) HEPATOTOXICITY and SKIN REACTIONS

See full prescribing information for complete boxed warning.

- Fatal and non-fatal hepatotoxicity (5.1)
- Fatal and non-fatal skin reactions (5.2)

Discontinue immediately if experiencing:

- Signs or symptoms of hepatitis (5.1)
- Increased transaminases combined with rash or other systemic symptoms (5.1)
- Severe skin or hypersensitivity reactions (5.2)
- Any rash with systemic symptoms (5.2)

Monitoring during the first 18 weeks of therapy is essential. Extra vigilance is warranted during the first 6 weeks of therapy, which is the period of greatest risk of these events (5) .

RECENT MAJOR CHANGES

Warnings and Precautions
Drug Interactions (5.4) 1/2010

1 INDICATIONS AND USAGE

- VIRAMUNE is an NNRTI indicated for combination antiretroviral treatment of HIV-1 infection (1)

Important Considerations:

- Initiation of treatment is not recommended in the following populations unless the benefits outweigh the risks (1, 5.1)
  - adult females with CD4^+ cell counts >250 cells/mm^3
  - adult males with CD4^+ cell counts >400 cells/mm^3
- The 14-day lead-in period must be strictly followed; it may reduce the frequency of rash (2.4, 5.2)

2 DOSAGE AND ADMINISTRATION

- Any patient experiencing rash during the 14-day lead-in period should not increase dose until the rash has resolved. The lead-in dosing regimen should not be continued beyond 28 days (2.4)
- If dosing interrupted for >7 days, restart 14-day lead-in dosing (2.4)

 | Adults (≥16 yrs) | Pediatric* (>15 days)
First 14 days | 200 mg once daily | 150 mg/m^2 once daily
After 14 days | 200 mg twice daily | 150 mg/m^2 twice daily
*Total daily dose should not exceed 400 mg for any patient.

3 DOSAGE FORMS AND STRENGTHS

- Tablets: 200 mg (3)
- Oral suspension: 50 mg/5 mL (3)

4 CONTRAINDICATIONS

- Patients with moderate or severe (Child-Pugh Class B or C, respectively) hepatic impairment (4, 5.1, 8.7)

5 WARNINGS AND PRECAUTIONS

- Hepatitis and hepatic failure (5)
- Stevens-Johnson syndrome (5)
- Toxic epidermal necrolysis (5)
- Hypersensitivity reactions (5)

6 ADVERSE REACTIONS

- The most common adverse reaction is rash. In adults the incidence of rash is 14.8% vs 5.9% with placebo, with Grade 3/4 rash occurring in 1.5% of patients (6.1)
- In pediatric patients the incidence of rash (all causality) was 21% (6.2)

To report SUSPECTED ADVERSE REACTIONS, contact Boehringer Ingelheim Pharmaceuticals, Inc. at (800) 542-6257 or (800) 459-9906 TTY, or FDA at 1-800-FDA-1088 or www.fda.gov/medwatch.

7 DRUG INTERACTIONS

Co-administration of VIRAMUNE can alter the concentrations of other drugs and other drugs may alter the concentration of nevirapine. The potential for drug interactions must be considered prior to and during therapy (7, 12.3)

8 USE IN SPECIFIC POPULATIONS

- Patients with hepatic fibrosis or cirrhosis should be monitored carefully for evidence of drug induced toxicity. Patients with Child-Pugh B or C should not receive VIRAMUNE (5.1, 8.7)
- No dose adjustment is required for patients with renal impairment. Patients on dialysis should receive an additional dose of 200 mg following each dialysis treatment (8.6)

FULL PRESCRIBING INFORMATION

WARNING: LIFE-THREATENING (INCLUDING FATAL) HEPATOTOXICITY and SKIN REACTIONS

HEPATOTOXICITY:

Severe, life-threatening, and in some cases fatal hepatotoxicity, particularly in the first 18 weeks, has been reported in patients treated with VIRAMUNE. In some cases, patients presented with non-specific prodromal signs or symptoms of hepatitis and progressed to hepatic failure. These events are often associated with rash. Female gender and higher CD4^+ cell counts at initiation of therapy place patients at increased risk; women with CD4^+ cell counts >250 cells/mm^3, including pregnant women receiving VIRAMUNE in combination with other antiretrovirals for the treatment of HIV-1 infection, are at the greatest risk. However, hepatotoxicity associated with VIRAMUNE use can occur in both genders, all CD4^+ cell counts and at any time during treatment. Patients with signs or symptoms of hepatitis, or with increased transaminases combined with rash or other systemic symptoms, must discontinue VIRAMUNE and seek medical evaluation immediately [see Warnings and Precautions (5.1)].

SKIN REACTIONS:

Severe, life-threatening skin reactions, including fatal cases, have occurred in patients treated with VIRAMUNE. These have included cases of Stevens-Johnson syndrome, toxic epidermal necrolysis, and hypersensitivity reactions characterized by rash, constitutional findings, and organ dysfunction. Patients developing signs or symptoms of severe skin reactions or hypersensitivity reactions must discontinue VIRAMUNE and seek medical evaluation immediately. Transaminase levels should be checked immediately for all patients who develop a rash in the first 18 weeks of treatment. The 14-day lead-in period with VIRAMUNE 200 mg daily dosing has been observed to decrease the incidence of rash and must be followed [see Warnings and Precautions (5.2)].

MONITORING:

Patients must be monitored intensively during the first 18 weeks of therapy with VIRAMUNE to detect potentially life-threatening hepatotoxicity or skin reactions. Extra vigilance is warranted during the first 6 weeks of therapy, which is the period of greatest risk of these events. Do not restart VIRAMUNE following severe hepatic, skin or hypersensitivity reactions. In some cases, hepatic injury has progressed despite discontinuation of treatment.

1 INDICATIONS AND USAGE

VIRAMUNE is indicated for use in combination with other antiretroviral agents for the treatment of HIV-1 infection. This indication is based on one principal clinical trial (BI 1090) that demonstrated prolonged suppression of HIV-1 RNA and two smaller supportive studies, one of which (BI 1046) is described below.

Additional important information regarding the use of VIRAMUNE for the treatment of HIV-1 infection:

- Based on serious and life-threatening hepatotoxicity observed in controlled and uncontrolled studies, VIRAMUNE should not be initiated in adult females with CD4^+ cell counts greater than 250 cells/mm^3 or in adult males with CD4^+ cell counts greater than 400 cells/mm^3 unless the benefit outweighs the risk [see Boxed Warning and Warnings and Precautions (5.1)].
- The 14-day lead-in period with VIRAMUNE 200 mg daily dosing has been demonstrated to reduce the frequency of rash [see Dosage and Administration (2.4) and Warnings and Precautions (5.2)].
- If rash persists beyond the 14-day lead-in period, do not dose escalate to 200 mg twice daily. The 200 mg once-daily dosing regimen should not be continued beyond 28 days, at which point an alternative regimen should be sought.

2 DOSAGE AND ADMINISTRATION

2.1 Adults

The recommended dose for VIRAMUNE is one 200 mg tablet daily for the first 14 days, followed by one 200 mg tablet twice daily, in combination with other antiretroviral agents. The lead-in period has been observed to decrease the incidence of rash. For concomitantly administered antiretroviral therapy, the manufacturer’s recommended dosage and monitoring should be followed.

2.2 Pediatric Patients

The recommended oral dose for pediatric patients 15 days and older is 150 mg/m^2 once daily for 14 days followed by 150 mg/m^2 twice daily thereafter. The total daily dose should not exceed 400 mg for any patient.

Table 1 Calculation of the Volume of VIRAMUNE Oral Suspension (50 mg/5 mL) Required for Pediatric Dosing Based on Body Surface and a Dose of 150 mg/m^2
BSA range (m^2) | Volume (mL)
0.06 – 0.12 | 1.25
0.12 – 0.25 | 2.5
0.25 – 0.42 | 5
0.42 – 0.58 | 7.5
0.58 – 0.75 | 10
0.75 – 0.92 | 12.5
0.92 – 1.08 | 15
1.08 – 1.25 | 17.5
1.25+ | 20

VIRAMUNE suspension should be shaken gently prior to administration. It is important to administer the entire measured dose of suspension by using an oral dosing syringe or dosing cup. An oral dosing syringe is recommended, particularly for volumes of 5 mL or less. If a dosing cup is used, it should be thoroughly rinsed with water and the rinse should also be administered to the patient.

2.3 Monitoring of Patients

Intensive clinical and laboratory monitoring, including liver enzyme tests, is essential at baseline and during the first 18 weeks of treatment with VIRAMUNE. The optimal frequency of monitoring during this period has not been established. Some experts recommend clinical and laboratory monitoring more often than once per month, and in particular, would include monitoring of liver enzyme tests at baseline, prior to dose escalation, and at two weeks post-dose escalation. After the initial 18-week period, frequent clinical and laboratory monitoring should continue throughout VIRAMUNE treatment [see Warnings and Precautions (5)]. In some cases, hepatic injury has progressed despite discontinuation of treatment.

2.4 Dosage Adjustment

Patients with Rash

VIRAMUNE should be discontinued if a patient experiences severe rash or any rash accompanied by constitutional findings [see Boxed Warning, Warnings and Precautions (5.2), and Patient Counseling Information (17.1)]. A patient experiencing mild to moderate rash without constitutional symptoms during the 14-day lead-in period of 200 mg/day (150 mg/m^2/day in pediatric patients) should not have their VIRAMUNE dose increased until the rash has resolved [see Warnings and Precautions (5.2) and Patient Counseling Information (17.1)]. The total duration of the once daily lead-in dosing period should not exceed 28 days at which point an alternative regimen should be sought.

Patients with Hepatic Events

If a clinical (symptomatic) hepatic event occurs, VIRAMUNE should be permanently discontinued. Do not restart VIRAMUNE after recovery [see Warnings and Precautions (5.1)].

Patients with Dose Interruption

Patients who interrupt VIRAMUNE dosing for more than 7 days should restart the recommended dosing, using one 200 mg tablet daily (150 mg/m^2/day in pediatric patients) for the first 14 days (lead-in) followed by one 200 mg tablet twice daily (150 mg/m^2 twice daily for pediatric patients).

Patients on Dialysis

An additional 200 mg dose of VIRAMUNE following each dialysis treatment is indicated in patients requiring dialysis. Nevirapine metabolites may accumulate in patients receiving dialysis; however, the clinical significance of this accumulation is not known [see Clinical Pharmacology (12.3)]. Patients with CrCL ≥20 mL/min do not require an adjustment in VIRAMUNE dosing.

3 DOSAGE FORMS AND STRENGTHS

Tablets: 200 mg, white, oval, biconvex, tablets embossed with 54 193 on one side
Oral suspension: 50 mg/5 mL, white to off-white oral suspension

4 CONTRAINDICATIONS

VIRAMUNE is contraindicated in patients with moderate or severe (Child-Pugh Class B or C, respectively) hepatic impairment [see Warnings and Precautions (5.1) and Use in Specific Populations (8.7)].

5 WARNINGS AND PRECAUTIONS

The most serious adverse reactions associated with VIRAMUNE are hepatitis/hepatic failure, Stevens-Johnson syndrome, toxic epidermal necrolysis, and hypersensitivity reactions. Hepatitis/hepatic failure may be associated with signs of hypersensitivity which can include severe rash or rash accompanied by fever, general malaise, fatigue, muscle or joint aches, blisters, oral lesions, conjunctivitis, facial edema, eosinophilia, granulocytopenia, lymphadenopathy, or renal dysfunction.

The first 18 weeks of therapy with VIRAMUNE are a critical period during which intensive clinical and laboratory monitoring of patients is required to detect potentially life-threatening hepatic events and skin reactions. The optimal frequency of monitoring during this time period has not been established. Some experts recommend clinical and laboratory monitoring more often than once per month, and in particular, would include monitoring of liver enzyme tests at baseline, prior to dose escalation and at two weeks post-dose escalation. After the initial 18-week period, frequent clinical and laboratory monitoring should continue throughout VIRAMUNE treatment. In addition, the 14-day lead-in period with VIRAMUNE 200 mg daily dosing has been demonstrated to reduce the frequency of rash [see Dosage and Administration (2.1)].

5.1 Hepatotoxicity and Hepatic Impairment

Severe, life-threatening, and in some cases fatal hepatotoxicity, including fulminant and cholestatic hepatitis, hepatic necrosis and hepatic failure, have been reported in patients treated with VIRAMUNE. In controlled clinical trials, symptomatic hepatic events regardless of severity occurred in 4% (range 0% to 11.0%) of patients who received VIRAMUNE and 1.2% of patients in control groups.

The risk of symptomatic hepatic events regardless of severity was greatest in the first 6 weeks of therapy. The risk continued to be greater in the VIRAMUNE groups compared to controls through 18 weeks of treatment. However, hepatic events may occur at any time during treatment. In some cases, patients presented with non-specific, prodromal signs or symptoms of fatigue, malaise, anorexia, nausea, jaundice, liver tenderness or hepatomegaly, with or without initially abnormal serum transaminase levels. Rash was observed in approximately half of the patients with symptomatic hepatic adverse events. Fever and flu-like symptoms accompanied some of these hepatic events. Some events, particularly those with rash and other symptoms, have progressed to hepatic failure with transaminase elevation, with or without hyperbilirubinemia, hepatic encephalopathy, prolonged partial thromboplastin time, or eosinophilia. Rhabdomyolysis has been observed in some patients experiencing skin and/or liver reactions associated with VIRAMUNE use. Patients with signs or symptoms of hepatitis must be advised to discontinue VIRAMUNE and immediately seek medical evaluation, which should include liver enzyme tests.

Transaminases should be checked immediately if a patient experiences signs or symptoms suggestive of hepatitis and/or hypersensitivity reaction. Transaminases should also be checked immediately for all patients who develop a rash in the first 18 weeks of treatment. Physicians and patients should be vigilant for the appearance of signs or symptoms of hepatitis, such as fatigue, malaise, anorexia, nausea, jaundice, bilirubinuria, acholic stools, liver tenderness or hepatomegaly. The diagnosis of hepatotoxicity should be considered in this setting, even if transaminases are initially normal or alternative diagnoses are possible [see Boxed Warning, Dosage and Administration (2.3), and Patient Counseling Information (17.1)].

If clinical hepatitis or transaminase elevations combined with rash or other systemic symptoms occur, VIRAMUNE should be permanently discontinued. Do not restart VIRAMUNE after recovery. In some cases, hepatic injury progresses despite discontinuation of treatment.

The patients at greatest risk of hepatic events, including potentially fatal events, are women with high CD4^+ cell counts. In general, during the first 6 weeks of treatment, women have a three-fold higher risk than men for symptomatic, often rash-associated, hepatic events (5.8% versus 2.2%), and patients with higher CD4^+ cell counts at initiation of VIRAMUNE therapy are at higher risk for symptomatic hepatic events with VIRAMUNE. In a retrospective review, women with CD4^+ cell counts >250 cells/mm^3 had a 12-fold higher risk of symptomatic hepatic adverse events compared to women with CD4^+ cell counts <250 cells/mm^3 (11.0% versus 0.9%). An increased risk was observed in men with CD4^+ cell counts >400 cells/mm^3 (6.3% versus 1.2% for men with CD4^+ cell counts <400 cells/mm^3). However, all patients, regardless of gender, CD4^+ cell count, or antiretroviral treatment history, should be monitored for hepatotoxicity since symptomatic hepatic adverse events have been reported at all CD4^+ cell counts. Co-infection with hepatitis B or C and/or increased transaminase elevations at the start of therapy with VIRAMUNE are associated with a greater risk of later symptomatic events (6 weeks or more after starting VIRAMUNE) and asymptomatic increases in AST or ALT.

In addition, serious hepatotoxicity (including liver failure requiring transplantation in one instance) has been reported in HIV-1 uninfected individuals receiving multiple doses of VIRAMUNE in the setting of post-exposure prophylaxis, an unapproved use.

Increased nevirapine trough concentrations have been observed in some patients with hepatic fibrosis or cirrhosis. Therefore, patients with either hepatic fibrosis or cirrhosis should be monitored carefully for evidence of drug-induced toxicity. Nevirapine should not be administered to patients with moderate or severe (Child-Pugh Class B or C, respectively) hepatic impairment [see Contraindications (4), Use in Specific Populations (8.7), and Clinical Pharmacology (12.3)].

5.2 Skin Reactions

Severe and life-threatening skin reactions, including fatal cases, have been reported, occurring most frequently during the first 6 weeks of therapy. These have included cases of Stevens-Johnson syndrome, toxic epidermal necrolysis, and hypersensitivity reactions characterized by rash, constitutional findings, and organ dysfunction including hepatic failure. Rhabdomyolysis has been observed in some patients experiencing skin and/or liver reactions associated with VIRAMUNE use. In controlled clinical trials, Grade 3 and 4 rashes were reported during the first 6 weeks in 1.5% of VIRAMUNE recipients compared to 0.1% of placebo subjects.

Patients developing signs or symptoms of severe skin reactions or hypersensitivity reactions (including, but not limited to, severe rash or rash accompanied by fever, general malaise, fatigue, muscle or joint aches, blisters, oral lesions, conjunctivitis, facial edema, and/or hepatitis, eosinophilia, granulocytopenia, lymphadenopathy, and renal dysfunction) must permanently discontinue VIRAMUNE and seek medical evaluation immediately [see Boxed Warning and Patient Counseling Information (17.1)]. Do not restart VIRAMUNE following severe skin rash, skin rash combined with increased transaminases or other symptoms, or hypersensitivity reaction.

If patients present with a suspected VIRAMUNE-associated rash, transaminases should be measured immediately. Patients with rash-associated transaminase elevations should be permanently discontinued from VIRAMUNE [see Warnings and Precautions (5.1)].

Therapy with VIRAMUNE must be initiated with a 14-day lead-in period of 200 mg/day (150 mg/m^2/day in pediatric patients), which has been shown to reduce the frequency of rash. VIRAMUNE should be discontinued if a patient experiences severe rash or any rash accompanied by constitutional findings. A patient experiencing a mild to moderate rash without constitutional symptoms during the 14-day lead-in period of 200 mg/day (150 mg/m^2/day in pediatric patients) should not have their VIRAMUNE dose increased until the rash has resolved. The total duration of the once-daily lead-in dosing period should not exceed 28 days at which point an alternative regimen should be sought [see Dosage and Administration (2.4)]. Patients should be monitored closely if isolated rash of any severity occurs. Delay in stopping VIRAMUNE treatment after the onset of rash may result in a more serious reaction.

Women appear to be at higher risk than men of developing rash with VIRAMUNE.

In a clinical trial, concomitant prednisone use (40 mg/day for the first 14 days of VIRAMUNE administration) was associated with an increase in incidence and severity of rash during the first 6 weeks of VIRAMUNE therapy. Therefore, use of prednisone to prevent VIRAMUNE-associated rash is not recommended.

5.3 Resistance

VIRAMUNE must not be used as a single agent to treat HIV-1 or added on as a sole agent to a failing regimen. Resistant virus emerges rapidly when nevirapine is administered as monotherapy. The choice of new antiretroviral agents to be used in combination with nevirapine should take into consideration the potential for cross resistance. When discontinuing an antiretroviral regimen containing VIRAMUNE, the long half-life of nevirapine should be taken into account; if antiretrovirals with shorter half-lives than VIRAMUNE are stopped concurrently, low plasma concentrations of nevirapine alone may persist for a week or longer and virus resistance may subsequently develop [see Clinical Pharmacology (12.4)].

5.4 Drug Interactions

See Table 4 for listings of established and potential drug interactions [see Drug Interactions (7)].

Concomitant use of St. John's wort (Hypericum perforatum) or St. John's wort-containing products and VIRAMUNE is not recommended. Co-administration of St. John’s wort with non-nucleoside reverse transcriptase inhibitors (NNRTIs), including VIRAMUNE, is expected to substantially decrease NNRTI concentrations and may result in sub-optimal levels of VIRAMUNE and lead to loss of virologic response and possible resistance to VIRAMUNE or to the class of NNRTIs. Co-administration of VIRAMUNE and efavirenz is not recommended as this combination has been associated with an increase in adverse reactions and no improvement in efficacy.

5.5 Immune Reconstitution Syndrome

Immune reconstitution syndrome has been reported in patients treated with combination antiretroviral therapy, including VIRAMUNE. During the initial phase of combination antiretroviral treatment, patients whose immune system responds may develop an inflammatory response to indolent or residual opportunistic infections (such as Mycobacterium avium infection, cytomegalovirus, Pneumocystis jiroveci pneumonia (PCP), or tuberculosis), which may necessitate further evaluation and treatment.

5.6 Fat Redistribution

Redistribution/accumulation of body fat including central obesity, dorsocervical fat enlargement (buffalo hump), peripheral wasting, facial wasting, breast enlargement, and "cushingoid appearance" have been observed in patients receiving antiretroviral therapy. The mechanism and long-term consequences of these events are currently unknown. A causal relationship has not been established.

6 ADVERSE REACTIONS

6.1 Clinical Trials in Adults

The most serious adverse reactions associated with VIRAMUNE are hepatitis, hepatic failure, Stevens-Johnson syndrome, toxic epidermal necrolysis, and hypersensitivity reactions. Hepatitis/hepatic failure may be isolated or associated with signs of hypersensitivity which may include severe rash or rash accompanied by fever, general malaise, fatigue, muscle or joint aches, blisters, oral lesions, conjunctivitis, facial edema, eosinophilia, granulocytopenia, lymphadenopathy, or renal dysfunction [see Boxed Warning and Warnings and Precautions (5.1, 5.2)].

Hepatic Reaction

In controlled clinical trials, symptomatic hepatic events regardless of severity occurred in 4.0% (range 0% to 11.0%) of patients who received VIRAMUNE and 1.2% of patients in control groups. Female gender and higher CD4^+ cell counts (>250 cells/mm^3 in women and >400 cells/mm^3 in men) place patients at increased risk of these events [see Boxed Warning and Warnings and Precautions (5.1)].

Asymptomatic transaminase elevations (AST or ALT >5X ULN) were observed in 5.8% (range 0% to 9.2%) of patients who received VIRAMUNE and 5.5% of patients in control groups. Co-infection with hepatitis B or C and/or increased transaminase elevations at the start of therapy with VIRAMUNE are associated with a greater risk of later symptomatic events (6 weeks or more after starting VIRAMUNE) and asymptomatic increases in AST or ALT.

Liver enzyme abnormalities (AST, ALT, GGT) were observed more frequently in patients receiving VIRAMUNE than in controls (see Table 3).

Skin Reaction

The most common clinical toxicity of VIRAMUNE is rash, which can be severe or life-threatening [see Boxed Warning and Warnings and Precautions (5.2)]. Rash occurs most frequently within the first 6 weeks of therapy. Rashes are usually mild to moderate, maculopapular erythematous cutaneous eruptions, with or without pruritus, located on the trunk, face and extremities. In controlled clinical trials (Trials 1037, 1038, 1046, and 1090), Grade 1 and 2 rashes were reported in 13.3% of patients receiving VIRAMUNE compared to 5.8% receiving placebo during the first 6 weeks of therapy. Grade 3 and 4 rashes were reported in 1.5% of VIRAMUNE recipients compared to 0.1% of subjects receiving placebo. Women tend to be at higher risk for development of VIRAMUNE-associated rash [see Boxed Warning and Warnings and Precautions (5.2)].

Because clinical trials are conducted under widely varying conditions, adverse reaction rates observed in the clinical trials of a drug cannot be directly compared to rates in the clinical trials of another drug and may not reflect the rates observed in practice.

Treatment-related, adverse experiences of moderate or severe intensity observed in >2% of patients receiving VIRAMUNE in placebo-controlled trials are shown in Table 2.

Table 2 Percentage of Patients with Moderate or Severe Drug-Related Events in Adult Placebo-Controlled Trials
 | Trial 1090^1 |  | Trials 1037, 1038, 1046^2
 | VIRAMUNE | Placebo | VIRAMUNE | Placebo
 | (n=1121) | (n=1128) | (n=253) | (n=203)
Median exposure (weeks) | 58 | 52 | 28 | 28
Any adverse event | 14.5% | 11.1% | 31.6% | 13.3%
Rash | 5.1 | 1.8 | 6.7 | 1.5
Nausea | 0.5 | 1.1 | 8.7 | 3.9
Granulocytopenia | 1.8 | 2.8 | 0.4 | 0
Headache | 0.7 | 0.4 | 3.6 | 0.5
Fatigue | 0.2 | 0.3 | 4.7 | 3.9
Diarrhea | 0.2 | 0.8 | 2.0 | 0.5
Abdominal pain | 0.1 | 0.4 | 2.0 | 0
Myalgia | 0.2 | 0 | 1.2 | 2.0
^1 Background therapy included 3TC for all patients and combinations of NRTIs and PIs. Patients had CD4^+ cell counts <200 cells/mm^3.
^2 Background therapy included ZDV and ZDV+ddI; VIRAMUNE monotherapy was administered in some patients. Patients had CD4^+ cell count ≥200 cells/mm^3.

Laboratory Abnormalities

Liver enzyme test abnormalities (AST, ALT) were observed more frequently in patients receiving VIRAMUNE than in controls (Table 3). Asymptomatic elevations in GGT occur frequently but are not a contraindication to continue VIRAMUNE therapy in the absence of elevations in other liver enzyme tests. Other laboratory abnormalities (bilirubin, anemia, neutropenia, thrombocytopenia) were observed with similar frequencies in clinical trials comparing VIRAMUNE and control regimens (see Table 3).

Table 3 Percentage of Adult Patients with Laboratory Abnormalities
 | Trial 1090^1 |  | Trials 1037, 1038, 1046^2
 | VIRAMUNE | Placebo | VIRAMUNE | Placebo
Laboratory Abnormality | (n=1121) | (n=1128) | (n=253) | (n=203)
Blood Chemistry
SGPT (ALT) >250 U/L | 5.3 | 4.4 | 14.0 | 4.0
SGOT (AST) >250 U/L | 3.7 | 2.5 | 7.6 | 1.5
Bilirubin >2.5 mg/dL | 1.7 | 2.2 | 1.7 | 1.5
Hematology
Hemoglobin <8.0 g/dL | 3.2 | 4.1 | 0 | 0
Platelets <50,000/mm^3 | 1.3 | 1.0 | 0.4 | 1.5
Neutrophils <750/mm^3 | 13.3 | 13.5 | 3.6 | 1.0
^1 Background therapy included 3TC for all patients and combinations of NRTIs and PIs. Patients had CD4^+ cell counts <200 cells/mm^3.
^2 Background therapy included ZDV and ZDV+ddI; VIRAMUNE monotherapy was administered in some patients. Patients had CD4^+ cell count >200 cells/mm^3.

6.2 Clinical Trials in Pediatric Patients

Adverse events were assessed in BI Trial 1100.1032 (ACTG 245), a double-blind, placebo-controlled trial of VIRAMUNE (n=305) in which pediatric patients received combination treatment with VIRAMUNE. In this trial two patients were reported to experience Stevens-Johnson syndrome or Stevens-Johnson/toxic epidermal necrolysis transition syndrome. Safety was also assessed in trial BI 1100.882 (ACTG 180), an open-label trial of VIRAMUNE (n=37) in which patients were followed for a mean duration of 33.9 months (range: 6.8 months to 5.3 years, including long-term follow-up in 29 of these patients in trial BI 1100.892). The most frequently reported adverse events related to VIRAMUNE in pediatric patients were similar to those observed in adults, with the exception of granulocytopenia, which was more commonly observed in children receiving both zidovudine and VIRAMUNE. Cases of allergic reaction, including one case of anaphylaxis, were also reported.

The safety of VIRAMUNE was also examined in BI Trial 1100.1368, an open-label, randomized clinical study performed in South Africa in which 123 HIV-1 infected treatment-naïve patients between 3 months and 16 years of age received combination treatment with VIRAMUNE oral suspension, lamivudine and zidovudine for 48 weeks [see Use In Specific Populations (8.4) and Clinical Pharmacology (12.3)]. Rash (all causality) was reported in 21% of the patients, 4 (3%) of whom discontinued drug due to rash. All 4 patients experienced the rash early in the course of therapy (<4 weeks) and resolved upon nevirapine discontinuation. Other clinically important adverse events (all causality) include neutropenia (8.9%), anemia (7.3%) and hepatotoxicity (2.4%) [see Use in Specific Populations (8.4) and Clinical Studies (14.2)].

Safety information on use of VIRAMUNE in combination therapy in pediatric patients 2 weeks to <3 months of age was assessed in 36 patients from the BI 1100.1222 (PACTG 356) study. No unexpected safety findings were observed although granulocytopenia was reported more frequently in this age group compared to the older pediatric age groups and adults.

6.3 Post-Marketing Surveillance

In addition to the adverse events identified during clinical trials, the following adverse reactions have been identified during post-approval use of VIRAMUNE. Because these reactions are reported voluntarily from a population of uncertain size, it is not always possible to reliably estimate their frequency or establish a causal relationship to drug exposure.

Body as a Whole: fever, somnolence, drug withdrawal [see Drug Interactions (7)], redistribution/accumulation of body fat [see Warnings and Precautions (5.6)]
Gastrointestinal: vomiting
Liver and Biliary: jaundice, fulminant and cholestatic hepatitis, hepatic necrosis, hepatic failure
Hematology: anemia, eosinophilia, neutropenia
Musculoskeletal: arthralgia, rhabdomyolysis associated with skin and/or liver reactions
Neurologic: paraesthesia
Skin and Appendages: allergic reactions including anaphylaxis, angioedema, bullous eruptions, ulcerative stomatitis and urticaria have all been reported. In addition, hypersensitivity syndrome and hypersensitivity reactions with rash associated with constitutional findings such as fever, blistering, oral lesions, conjunctivitis, facial edema, muscle or joint aches, general malaise, fatigue or significant hepatic abnormalities [see Warnings and Precautions (5.1)] plus one or more of the following: hepatitis, eosinophilia, granulocytopenia, lymphadenopathy and/or renal dysfunction have been reported with the use of VIRAMUNE.

In post-marketing surveillance anemia has been more commonly observed in children although development of anemia due to concomitant medication use cannot be ruled out.

7 DRUG INTERACTIONS

Nevirapine is principally metabolized by the liver via the cytochrome P450 isoenzymes, 3A and 2B6. Nevirapine is known to be an inducer of these enzymes. As a result, drugs that are metabolized by these enzyme systems may have lower than expected plasma levels when co-administered with nevirapine.

The specific pharmacokinetic changes that occur with co-administration of nevirapine and other drugs are listed in Clinical Pharmacology, Table 5. Clinical comments about possible dosage modifications based on established drug interactions are listed in Table 4. The data in Tables 4 and 5 are based on the results of drug interaction studies conducted in HIV-1 seropositive subjects unless otherwise indicated. In addition to established drug interactions, there may be potential pharmacokinetic interactions between nevirapine and other drug classes that are metabolized by the cytochrome P450 system. These potential drug interactions are also listed in Table 4. Although specific drug interaction studies in HIV-1 seropositive subjects have not been conducted for some classes of drugs listed in Table 4, additional clinical monitoring may be warranted when co-administering these drugs.

The in vitro interaction between nevirapine and the antithrombotic agent warfarin is complex. As a result, when giving these drugs concomitantly, plasma warfarin levels may change with the potential for increases in coagulation time. When warfarin is co-administered with nevirapine, anticoagulation levels should be monitored frequently.

Table 4 Established and Potential Drug Interactions: Use With Caution, Alteration in Dose or Regimen May Be Needed Due to Drug Interaction Established Drug Interactions: See Clinical Pharmacology (12.3), Table 5 for Magnitude of Interaction.
Drug Name | Effect on Concentration of Nevirapine or Concomitant Drug | Clinical Comment
Atazanavir/Ritonavir | ↓ Atazanavir ↑ Nevirapine | Do not co-administer nevirapine with atazanavir because nevirapine substantially decreases atazanavir exposure.
Clarithromycin | ↓ Clarithromycin ↑ 14-OH clarithromycin | Clarithromycin exposure was significantly decreased by nevirapine; however, 14-OH metabolite concentrations were increased. Because clarithromycin active metabolite has reduced activity against Mycobacterium avium-intracellulare complex, overall activity against this pathogen may be altered. Alternatives to clarithromycin, such as azithromycin, should be considered.
Efavirenz | ↓ Efavirenz | There has been no determination of appropriate doses for the safe and effective use of this combination [see Warnings and Precautions (5.4)].
Ethinyl estradiol and Norethindrone | ↓ Ethinyl estradiol ↓ Norethindrone | Oral contraceptives and other hormonal methods of birth control should not be used as the sole method of contraception in women taking nevirapine, since nevirapine may lower the plasma levels of these medications. An alternative or additional method of contraception is recommended.
Fluconazole | ↑Nevirapine | Because of the risk of increased exposure to nevirapine, caution should be used in concomitant administration, and patients should be monitored closely for nevirapine-associated adverse events.
Fosamprenavir | ↓ Amprenavir ↑ Nevirapine | Co-administration of nevirapine and fosamprenavir without ritonavir is not recommended.
Fosamprenavir/Ritonavir | ↓ Amprenavir ↑ Nevirapine | No dosing adjustments are required when nevirapine is co-administered with 700/100 mg of fosamprenavir/ritonavir twice daily.
Indinavir | ↓ Indinavir | Appropriate doses for this combination are not established, but an increase in the dosage of indinavir may be required.
Ketoconazole | ↓ Ketoconazole | Nevirapine and ketoconazole should not be administered concomitantly because decreases in ketoconazole plasma concentrations may reduce the efficacy of the drug.
Lopinavir/Ritonavir | ↓Lopinavir | Lopinavir/ritonavir 400/100 mg tablets can be used twice daily in combination with nevirapine with no dose adjustment in antiretroviral-naïve patients. A dose increase of lopinavir/ritonavir tablets to 600/150 mg (3 tablets) twice daily may be considered when used in combination with nevirapine in treatment-experienced patients where decreased susceptibility to lopinavir is clinically suspected (by treatment history or laboratory evidence). A dose increase of lopinavir/ritonavir oral solution to 533/133 mg twice daily with food is recommended in combination with nevirapine. In children 6 months to 12 years of age, consideration should be given to increasing the dose of lopinavir/ritonavir to 13/3.25 mg/kg for those 7 to <15 kg; 11/2.75 mg/kg for those 15 to 45 kg; and up to a maximum dose of 533/133 mg for those >45 kg twice daily when used in combination with nevirapine, particularly for patients in whom reduced susceptibility to lopinavir/ritonavir is suspected.
Methadone | ↓ Methadone | Methadone levels were decreased; increased dosages may be required to prevent symptoms of opiate withdrawal. Methadone-maintained patients beginning nevirapine therapy should be monitored for evidence of withdrawal and methadone dose should be adjusted accordingly.
Nelfinavir | ↓Nelfinavir M8 Metabolite ↓Nelfinavir Cmin | The appropriate dose for nelfinavir in combination with nevirapine, with respect to safety and efficacy, has not been established.
Rifabutin | ↑Rifabutin | Rifabutin and its metabolite concentrations were moderately increased. Due to high intersubject variability, however, some patients may experience large increases in rifabutin exposure and may be at higher risk for rifabutin toxicity. Therefore, caution should be used in concomitant administration.
Rifampin | ↓ Nevirapine | Nevirapine and rifampin should not be administered concomitantly because decreases in nevirapine plasma concentrations may reduce the efficacy of the drug. Physicians needing to treat patients co-infected with tuberculosis and using a nevirapine-containing regimen may use rifabutin instead.
Saquinavir/ritonavir | The interaction between VIRAMUNE and saquinavir/ritonavir has not been evaluated | The appropriate doses of the combination of nevirapine and saquinavir/ritonavir with respect to safety and efficacy have not been established.
Potential Drug Interactions:
Drug Class | Examples of Drugs
Antiarrhythmics | Amiodarone, disopyramide, lidocaine | Plasma concentrations may be decreased.
Anticonvulsants | Carbamazepine, clonazepam, ethosuximide | Plasma concentrations may be decreased.
Antifungals | Itraconazole | Plasma concentrations of some azole antifungals may be decreased. Nevirapine and itraconazole should not be administered concomitantly due to a potential decrease in itraconazole plasma concentrations.
Calcium channel blockers | Diltiazem, nifedipine, verapamil | Plasma concentrations may be decreased.
Cancer chemotherapy | Cyclophosphamide | Plasma concentrations may be decreased.
Ergot alkaloids | Ergotamine | Plasma concentrations may be decreased.
Immunosuppressants | Cyclosporin, tacrolimus, sirolimus | Plasma concentrations may be decreased.
Motility agents | Cisapride | Plasma concentrations may be decreased.
Opiate agonists | Fentanyl | Plasma concentrations may be decreased.
Antithrombotics | Warfarin | Plasma concentrations may be increased. Potential effect on anticoagulation. Monitoring of anticoagulation levels is recommended.

8 USE IN SPECIFIC POPULATIONS

Teratogenic Effects, Pregnancy Category B.

No observable teratogenicity was detected in reproductive studies performed in pregnant rats and rabbits. The maternal and developmental no-observable-effect level dosages produced systemic exposures approximately equivalent to or approximately 50% higher in rats and rabbits, respectively, than those seen at the recommended daily human dose (based on AUC). In rats, decreased fetal body weights were observed due to administration of a maternally toxic dose (exposures approximately 50% higher than that seen at the recommended human clinical dose).

There are no adequate and well-controlled studies of VIRAMUNE in pregnant women. The Antiretroviral Pregnancy Registry, which has been surveying pregnancy outcomes since January 1989, has not found an increased risk of birth defects following first trimester exposures to nevirapine. The prevalence of birth defects after any trimester exposure to nevirapine is comparable to the prevalence observed in the general population.

Severe hepatic events, including fatalities, have been reported in pregnant women receiving chronic VIRAMUNE therapy as part of combination treatment of HIV-1 infection. Regardless of pregnancy status, women with CD4^+ cell counts >250 cells/mm^3 should not initiate VIRAMUNE unless the benefit outweighs the risk. It is unclear if pregnancy augments the risk observed in non-pregnant women [see Boxed Warning].

VIRAMUNE should be used during pregnancy only if the potential benefit justifies the potential risk to the fetus.

Antiretroviral Pregnancy Registry

To monitor maternal-fetal outcomes of pregnant women exposed to VIRAMUNE, an Antiretroviral Pregnancy Registry has been established. Physicians are encouraged to register patients by calling (800) 258-4263.

8.3 Nursing Mothers

The Centers for Disease Control and Prevention recommend that HIV-1 infected mothers not breastfeed their infants to avoid risking postnatal transmission of HIV-1. Nevirapine is excreted in breast milk. Because of both the potential for HIV-1 transmission and the potential for serious adverse reactions in nursing infants, mothers should be instructed not to breastfeed if they are receiving VIRAMUNE.

8.4 Pediatric Use

The safety, pharmacokinetic profile, and virologic and immunologic responses of VIRAMUNE have been evaluated in HIV-1 infected pediatric patients age 3 months to 18 years [see Adverse Reactions (6.2) and Clinical Studies (14.2)]. The safety and pharmacokinetic profile of VIRAMUNE has been evaluated in HIV-1 infected pediatric patients age 15 days to <3 months [see Adverse Reactions (6.2) and Clinical Studies (14.2)].

The most frequently reported adverse events related to VIRAMUNE in pediatric patients were similar to those observed in adults, with the exception of granulocytopenia, which was more commonly observed in children receiving both zidovudine and VIRAMUNE [see Adverse Reactions (6.2) and Clinical Studies (14.2)].

8.5 Geriatric Use

Clinical studies of VIRAMUNE did not include sufficient numbers of subjects aged 65 and older to determine whether elderly subjects respond differently from younger subjects. In general, dose selection for an elderly patient should be cautious, reflecting the greater frequency of decreased hepatic, renal or cardiac function, and of concomitant disease or other drug therapy.

8.6 Renal Impairment

In subjects with renal impairment (mild, moderate or severe), there were no significant changes in the pharmacokinetics of nevirapine. Nevirapine is extensively metabolized by the liver and nevirapine metabolites are extensively eliminated by the kidney. Nevirapine metabolites may accumulate in patients receiving dialysis; however, the clinical significance of this accumulation is not known. No adjustment in nevirapine dosing is required in patients with CrCL ≥20 mL/min. In patients undergoing chronic hemodialysis, an additional 200 mg dose following each dialysis treatment is indicated [see Dosage and Administration (2.4) and Clinical Pharmacology (12.3)].

8.7 Hepatic Impairment

Because increased nevirapine levels and nevirapine accumulation may be observed in patients with serious liver disease, do not administer VIRAMUNE to patients with moderate or severe (Child-Pugh Class B or C, respectively) hepatic impairment [see Contraindications (4), Warnings and Precautions (5.1), and Clinical Pharmacology (12.3)].

10 OVERDOSAGE

There is no known antidote for VIRAMUNE overdosage. Cases of VIRAMUNE overdose at doses ranging from 800 to 1800 mg per day for up to 15 days have been reported. Patients have experienced events including edema, erythema nodosum, fatigue, fever, headache, insomnia, nausea, pulmonary infiltrates, rash, vertigo, vomiting and weight decrease. All events subsided following discontinuation of VIRAMUNE.

11 DESCRIPTION

VIRAMUNE is the brand name for nevirapine, a non-nucleoside reverse transcriptase inhibitor (NNRTI) with activity against Human Immunodeficiency Virus Type 1 (HIV-1). Nevirapine is structurally a member of the dipyridodiazepinone chemical class of compounds.

The chemical name of nevirapine is 11-cyclopropyl-5,11-dihydro-4-methyl-6H-dipyrido [3,2-b:2',3'-e][1,4] diazepin-6-one. Nevirapine is a white to off-white crystalline powder with the molecular weight of 266.30 and the molecular formula C15H14N4O. Nevirapine has the following structural formula:

VIRAMUNE Tablets are for oral administration. Each tablet contains 200 mg of nevirapine and the inactive ingredients microcrystalline cellulose, lactose monohydrate, povidone, sodium starch glycolate, colloidal silicon dioxide and magnesium stearate.

VIRAMUNE Oral Suspension is for oral administration. Each 5 mL of VIRAMUNE suspension contains 50 mg of nevirapine (as nevirapine hemihydrate). The suspension also contains the following excipients: carbomer 934P, methylparaben, propylparaben, sorbitol, sucrose, polysorbate 80, sodium hydroxide and purified water.

12 CLINICAL PHARMACOLOGY

12.1 Mechanism of Action

Nevirapine is an antiviral drug [see Clinical Pharmacology (12.4)].

PHARMACODYNAMICS

Absorption and Bioavailability

Nevirapine is readily absorbed (>90%) after oral administration in healthy volunteers and in adults with HIV-1 infection. Absolute bioavailability in 12 healthy adults following single-dose administration was 93 ± 9% (mean ± SD) for a 50 mg tablet and 91 ± 8% for an oral solution. Peak plasma nevirapine concentrations of 2 ± 0.4 μg/mL (7.5 μM) were attained by 4 hours following a single 200 mg dose. Following multiple doses, nevirapine peak concentrations appear to increase linearly in the dose range of 200 to 400 mg/day. Steady-state trough nevirapine concentrations of 4.5 ± 1.9 μg/mL (17 ± 7 μM), (n = 242) were attained at 400 mg/day. Nevirapine tablets and suspension have been shown to be comparably bioavailable and interchangeable at doses up to 200 mg. When VIRAMUNE (200 mg) was administered to 24 healthy adults (12 female, 12 male), with either a high-fat breakfast (857 kcal, 50 g fat, 53% of calories from fat) or antacid (Maalox® 30 mL), the extent of nevirapine absorption (AUC) was comparable to that observed under fasting conditions. In a separate study in HIV-1 infected patients (n=6), nevirapine steady-state systemic exposure (AUCτ) was not significantly altered by didanosine, which is formulated with an alkaline buffering agent. VIRAMUNE may be administered with or without food, antacid or didanosine.

Distribution

Nevirapine is highly lipophilic and is essentially nonionized at physiologic pH. Following intravenous administration to healthy adults, the apparent volume of distribution (Vdss) of nevirapine was 1.21 ± 0.09 L/kg, suggesting that nevirapine is widely distributed in humans. Nevirapine readily crosses the placenta and is also found in breast milk [see Use In Specific Populations (8.3)]. Nevirapine is about 60% bound to plasma proteins in the plasma concentration range of 1-10 μg/mL. Nevirapine concentrations in human cerebrospinal fluid (n=6) were 45% (±5%) of the concentrations in plasma; this ratio is approximately equal to the fraction not bound to plasma protein.

Metabolism/Elimination

In vivo studies in humans and in vitro studies with human liver microsomes have shown that nevirapine is extensively biotransformed via cytochrome P450 (oxidative) metabolism to several hydroxylated metabolites. In vitro studies with human liver microsomes suggest that oxidative metabolism of nevirapine is mediated primarily by cytochrome P450 (CYP) isozymes from the CYP3A and CYP2B6 families, although other isozymes may have a secondary role. In a mass balance/excretion study in eight healthy male volunteers dosed to steady state with nevirapine 200 mg given twice daily followed by a single 50 mg dose of ^14C-nevirapine, approximately 91.4 ± 10.5% of the radiolabeled dose was recovered, with urine (81.3 ± 11.1%) representing the primary route of excretion compared to feces (10.1 ± 1.5%). Greater than 80% of the radioactivity in urine was made up of glucuronide conjugates of hydroxylated metabolites. Thus cytochrome P450 metabolism, glucuronide conjugation, and urinary excretion of glucuronidated metabolites represent the primary route of nevirapine biotransformation and elimination in humans. Only a small fraction (<5%) of the radioactivity in urine (representing <3% of the total dose) was made up of parent compound; therefore, renal excretion plays a minor role in elimination of the parent compound.

Nevirapine is an inducer of hepatic cytochrome P450 (CYP) metabolic enzymes 3A and 2B6. Nevirapine induces CYP3A and CYP2B6 by approximately 20-25%, as indicated by erythromycin breath test results and urine metabolites. Autoinduction of CYP3A and CYP2B6 mediated metabolism leads to an approximately 1.5- to 2-fold increase in the apparent oral clearance of nevirapine as treatment continues from a single dose to two-to-four weeks of dosing with 200-400 mg/day. Autoinduction also results in a corresponding decrease in the terminal phase half-life of nevirapine in plasma, from approximately 45 hours (single dose) to approximately 25-30 hours following multiple dosing with 200-400 mg/day.

Renal Impairment

HIV-1 seronegative adults with mild (CrCL 50-79 mL/min; n=7), moderate (CrCL 30-49 mL/min; n=6), or severe (CrCL <30 mL/min; n=4) renal impairment received a single 200 mg dose of nevirapine in a pharmacokinetic study. These subjects did not require dialysis. The study included six additional subjects with renal failure requiring dialysis.

In subjects with renal impairment (mild, moderate or severe), there were no significant changes in the pharmacokinetics of nevirapine. However, subjects requiring dialysis exhibited a 44% reduction in nevirapine AUC over a one-week exposure period. There was also evidence of accumulation of nevirapine hydroxy-metabolites in plasma in subjects requiring dialysis. An additional 200 mg dose following each dialysis treatment is indicated [see Dosage and Administration (2.4) and Use in Specific Populations (8.6)].

Hepatic Impairment

In a steady-state study comparing 46 patients with mild (n=17; expansion of some portal areas; Ishak Score 1-2), moderate (n=20; expansion of most portal areas with occasional portal-to-portal and portal-to-central bridging; Ishak Score 3-4), or severe (n=9; marked bridging with occasional cirrhosis without decompensation indicating Child-Pugh A; Ishak Score 5-6) fibrosis as a measure of hepatic impairment, the multiple dose pharmacokinetic disposition of nevirapine and its five oxidative metabolites were not altered. However, approximately 15% of these patients with hepatic fibrosis had nevirapine trough concentrations above 9,000 μg/mL (2-fold the usual mean trough). Therefore, patients with hepatic impairment should be monitored carefully for evidence of drug-induced toxicity [see Warnings and Precautions (5.1)]. The patients studied were receiving antiretroviral therapy containing VIRAMUNE 200 mg twice daily for at least 6 weeks prior to pharmacokinetic sampling, with a median duration of therapy of 3.4 years.

In a pharmacokinetic study where HIV-1 negative cirrhotic patients with mild (Child-Pugh A; n=6) or moderate (Child-Pugh B; n=4) hepatic impairment received a single 200 mg dose of nevirapine, a significant increase in the AUC of nevirapine was observed in one patient with Child-Pugh B and ascites suggesting that patients with worsening hepatic function and ascites may be at risk of accumulating nevirapine in the systemic circulation. Because nevirapine induces its own metabolism with multiple dosing, this single-dose study may not reflect the impact of hepatic impairment on multiple-dose pharmacokinetics.

Do not administer nevirapine to patients with moderate or severe (Child-Pugh Class B or C, respectively) hepatic impairment [see Contraindications (4), Warnings and Precautions (5.1), and Use in Specific Populations (8.7)].

Gender

In the multinational 2NN study, a population pharmacokinetic substudy of 1077 patients was performed that included 391 females. Female patients showed a 13.8% lower clearance of nevirapine than did men. Since neither body weight nor Body Mass Index (BMI) had an influence on the clearance of nevirapine, the effect of gender cannot solely be explained by body size.

Race

An evaluation of nevirapine plasma concentrations (pooled data from several clinical trials) from HIV-1-infected patients (27 Black, 24 Hispanic, 189 Caucasian) revealed no marked difference in nevirapine steady-state trough concentrations (median Cminss = 4.7 μg/mL Black, 3.8 μg/mL Hispanic, 4.3 μg/mL Caucasian) with long-term nevirapine treatment at 400 mg/day. However, the pharmacokinetics of nevirapine have not been evaluated specifically for the effects of ethnicity.

Geriatric Patients

Nevirapine pharmacokinetics in HIV-1-infected adults do not appear to change with age (range 18–68 years); however, nevirapine has not been extensively evaluated in patients beyond the age of 55 years [see Use in Specific Populations (8.5)].

Pediatric Patients

Pharmacokinetic data for nevirapine have been derived from two sources: a 48-week pediatric trial in South Africa (BI Trial 1100.1368) involving 123 HIV-1 positive, antiretroviral-naïve patients aged 3 months to 16 years; and a consolidated analysis of five Pediatric AIDS Clinical Trials Group (PACTG) protocols comprising 495 patients aged 14 days to 19 years.

BI Trial 1100.1368 studied the safety, efficacy, and pharmacokinetics of a weight-based and a body surface area (BSA)-based dosing regimen of nevirapine. In the weight-based regimen, pediatric patients up to 8 years of age received a dose of 4 mg/kg once daily for two weeks followed by 7 mg/kg twice daily thereafter. Patients 8 years and older were dosed 4 mg/kg once daily for two weeks followed by 4 mg/kg twice daily thereafter. In the BSA regimen, all pediatric patients received 150 mg/m^2 once daily for two weeks followed by 150 mg/m^2 twice daily thereafter [see Use In Specific Populations (8.4) and Adverse Reactions (6.2)]. Dosing of nevirapine at 150 mg/m^2 BID (after a two-week lead-in of 150 mg/m^2 QD) produced geometric mean or mean trough nevirapine concentrations between 4-6 μg/mL (as targeted from adult data). In addition, the observed trough nevirapine concentrations were comparable between the two dosing regimens studied (BSA- and weight-based methods).

The consolidated analysis of Pediatric AIDS Clinical Trials Group (PACTG) protocols 245, 356, 366, 377, and 403 allowed for the evaluation of pediatric patients less than 3 months of age (n=17). The plasma nevirapine concentrations observed were within the range observed in adults and the remainder of the pediatric population, but were more variable between patients, particularly in the second month of age. For dose recommendations for pediatric patients [see Dosage and Administration (2.2)].

Drug Interactions [see Drug Interactions (7)]

Nevirapine induces hepatic cytochrome P450 metabolic isoenzymes 3A and 2B6. Co-administration of VIRAMUNE and drugs primarily metabolized by CYP3A or CYP2B6 may result in decreased plasma concentrations of these drugs and attenuate their therapeutic effects.

While primarily an inducer of cytochrome P450 3A and 2B6 enzymes, nevirapine may also inhibit this system. Among human hepatic cytochrome P450s, nevirapine was capable in vitro of inhibiting the 10-hydroxylation of (R)-warfarin (CYP3A). The estimated Ki for the inhibition of CYP3A was 270 μM, a concentration that is unlikely to be achieved in patients as the therapeutic range is <25 μM. Therefore, nevirapine may have minimal inhibitory effect on other substrates of CYP3A.

Nevirapine does not appear to affect the plasma concentrations of drugs that are substrates of other CYP450 enzyme systems, such as 1A2, 2D6, 2A6, 2E1, 2C9 or 2C19.

Table 5 (see below) contains the results of drug interaction studies performed with VIRAMUNE and other drugs likely to be co-administered. The effects of VIRAMUNE on the AUC, Cmax, and Cmin of co-administered drugs are summarized.

Table 5 Drug Interactions: Changes in Pharmacokinetic Parameters for Co-administered Drug in the Presence of VIRAMUNE (All interaction studies were conducted in HIV-1 positive patients)
Co-administered Drug | Dose of Co-administered Drug | Dose Regimen of VIRAMUNE | n | % Change of Co-administered Drug Pharmacokinetic Parameters (90% CI)
Antiretrovirals |  |  |  | AUC | Cmax | Cmin
Atazanavir/Ritonavira,d | 300/100 mg QD day 4–13, then 400/100 mg QD, day 14–23 | 200 mg BID day 1-23. Subjects were treated with nevirapine prior to study entry. | 23 | Atazanavir 300/100 mg ↓42 (↓52 to ↓29) | Atazanavir 300/100 mg ↓28 (↓40 to ↓14) | Atazanavir 300/100 mg ↓72 (↓80 to ↓60)
Atazanavir/Ritonavira,d | 300/100 mg QD day 4–13, then 400/100 mg QD, day 14–23 | 200 mg BID day 1-23. Subjects were treated with nevirapine prior to study entry. | 23 | Atazanavir 400/100 mg ↓19 (↓35 to ↑2) | Atazanavir 400/100 mg ↑2 (↓15 to ↑24) | Atazanavir 400/100 mg ↓59 (↓73 to ↓40)
Darunavir/Ritonavire | 400/100 mg BID | 200 mg BID | 8 | ↑24 (↓3 to ↑57) | ↑40 (↑14 to ↑73) | ↑2 (↓21 to ↑32)
Didanosine | 100-150 mg BID | 200 mg QD x 14 days; 200 mg BID x 14 days | 18 | ⇔ | ⇔ | §
Efavirenza | 600 mg QD | 200 mg QD x 14 days; 400 mg QD x 14 days | 17 | ↓28 (↓34 to ↓14) | ↓12 (↓23 to ↑1) | ↓32 (↓35 to ↓19)
Fosamprenavir | 1400 mg BID | 200 mg BID. Subjects were treated with nevirapine prior to study entry. | 17 | ↓33 (↓45 to ↓20) | ↓25 (↓37 to ↓10) | ↓35 (↓50 to ↓15)
Fosamprenavir/Ritonavir | 700/100 mg BID | 200 mg BID. Subjects were treated with nevirapine prior to study entry | 17 | ↓11 (↓23 to ↑3) | ⇔ | ↓19 (↓32 to ↓4)
Indinavira | 800 mg q8H | 200 mg QD x 14 days; 200 mg BID x 14 days | 19 | ↓31 (↓39 to ↓22) | ↓15 (↓24 to ↓4) | ↓44 (↓53 to ↓33)
Lopinavira, b | 300/75 mg/m^2 (lopinavir/ ritonavir) b | 7 mg/kg or 4 mg/kg QD x 2 weeks; BID x 1 week | 12, 15 c | ↓22 (↓44 to ↑9) | ↓14 (↓36 to ↑16) | ↓55 (↓75 to ↓19)
Lopinavira | 400/100 mg BID (lopinavir/ ritonavir) | 200 mg QD x 14 days; 200 mg BID >1 year | 22, 19 c | ↓27 (↓47 to ↓2) | ↓19 (↓38 to ↑5) | ↓51 (↓72 to ↓26)
Maravirocf | 300 mg SD | 200 mg BID | 8 | ↑1 (↓35 to ↑55) | ↑54 (↓6 to ↑151) | ⇔
Nelfinavira | 750 mg TID | 200 mg QD x 14 days; 200 mg BID x 14 days | 23 | ⇔ | ⇔ | ↓32 (↓50 to ↑5)
Nelfinavir-M8 metabolite |  |  |  | ↓62 (↓70 to ↓53) | ↓59 (↓68 to ↓48) | ↓66 (↓74 to ↓55)
Ritonavir | 600 mg BID | 200 mg QD x 14 days; 200 mg BID x 14 days | 18 | ⇔ | ⇔ | ⇔
Stavudine | 30-40 mg BID | 200 mg QD x 14 days; 200 mg BID x 14 days | 22 | ⇔ | ⇔ | §
Zalcitabine | 0.125-0.25 mg TID | 200 mg QD x 14 days; 200 mg BID x 14 days | 6 | ⇔ | ⇔ | §
Zidovudine | 100-200 mg TID | 200 mg QD x 14 days; 200 mg BID x 14 days | 11 | ↓28 (↓40 to ↓4) | ↓30 (↓51 to ↑14) | §
Other Medications |  |  |  | AUC | Cmax | Cmin
Clarithromycina | 500 mg BID | 200 mg QD x 14 days; 200 mg BID x 14 days | 15 | ↓31 (↓38 to ↓24) | ↓23 (↓31 to ↓14) | ↓56 (↓70 to ↓36)
Metabolite 14-OH-clarithromycin |  |  |  | ↑42 (↑16 to ↑73) | ↑47 (↑21 to ↑80) | ⇔
Ethinyl estradiola and Norethindronea | 0.035 mg (as Ortho-Novum® 1/35) | 200 mg QD x 14 days; 200 mg BID x 14 days | 10 | ↓20 (↓33 to ↓3) | ⇔ | §
Ethinyl estradiola and Norethindronea | 1 mg (as Ortho-Novum® 1/35) | 200 mg QD x 14 days; 200 mg BID x 14 days | 10 | ↓19 (↓30 to ↓7) | ↓16 (↓27 to ↓3) | §
Depomedroxy-progesterone acetate | 150 mg every 3 months | 200 mg QD x 14 days; 200 mg BID x 14 days | 32 | ⇔ | ⇔ | ⇔
Fluconazole | 200 mg QD | 200 mg QD x 14 days; 200 mg BID x 14 days | 19 | ⇔ | ⇔ | ⇔
Ketoconazolea | 400 mg QD | 200 mg QD x 14 days; 200 mg BID x 14 days | 21 | ↓72 (↓80 to ↓60) | ↓44 (↓58 to ↓27) | §
Methadonea | Individual Patient Dosing | 200 mg QD x 14 days; 200 mg BID ≥7 days | 9 | In a controlled pharmacokinetic study with 9 patients receiving chronic methadone to whom steady-state nevirapine therapy was added, the clearance of methadone was increased by 3-fold, resulting in symptoms of withdrawal, requiring dose adjustments in 10 mg segments, in 7 of the 9 patients. Methadone did not have any effect on nevirapine clearance.
Rifabutina | 150 or 300 mg QD | 200 mg QD x 14 days; 200 mg BID x 14 days | 19 | ↑17 (↓2 to ↑40) | ↑28 (↑9 to ↑51) | ⇔
Metabolite 25-O-desacetyl-rifabutin |  |  |  | ↑24 (↓16 to ↑84) | ↑29 (↓2 to ↑68) | ↑22 (↓14 to ↑74)
Rifampina | 600 mg QD | 200 mg QD x 14 days; 200 mg BID x 14 days | 14 | ↑11 (↓4 to ↑28) | ⇔ | §
§ = Cmin below detectable level of the assay
↑ = Increase, ↓ = Decrease, ⇔ = No Effect
a For information regarding clinical recommendations, see Drug Interactions (7).
b Pediatric subjects ranging in age from 6 months to 12 years
c Parallel group design; n for VIRAMUNE+lopinavir/ritonavir, n for lopinavir/ritonavir alone.
d Parallel group design; n=23 for atazanavir/ritonavir + nevirapine, n=22 for atazanavir/ritonavir without nevirapine. Changes in atazanavir PK are relative to atazanavir/ritonavir 300/100 mg alone.
e Based on between-study comparison.
f Based on historical controls.

Because of the design of the drug interaction trials (addition of 28 days of VIRAMUNE therapy to existing HIV-1 therapy), the effect of the concomitant drug on plasma nevirapine steady-state concentrations was estimated by comparison to historical controls.

Administration of rifampin had a clinically significant effect on nevirapine pharmacokinetics, decreasing AUC and Cmax by greater than 50%. Administration of fluconazole resulted in an approximate 100% increase in nevirapine exposure, based on a comparison to historic data [see Drug Interactions (7)]. The effect of other drugs listed in Table 5 on nevirapine pharmacokinetics was not significant. No significant interaction was observed when tipranavir was co-administered with low-dose ritonavir and nevirapine.

Mechanism of Action

Nevirapine is a non-nucleoside reverse transcriptase inhibitor (NNRTI) of HIV-1. Nevirapine binds directly to reverse transcriptase (RT) and blocks the RNA-dependent and DNA-dependent DNA polymerase activities by causing a disruption of the enzyme's catalytic site. The activity of nevirapine does not compete with template or nucleoside triphosphates. HIV-2 RT and eukaryotic DNA polymerases (such as human DNA polymerases α, β, γ, or δ) are not inhibited by nevirapine.

Antiviral Activity

The antiviral activity of nevirapine has been measured in a variety of cell lines including peripheral blood mononuclear cells, monocyte-derived macrophages, and lymphoblastoid cell lines. In an assay using human embryonic kidney 293 cells, the median EC50 value (50% inhibitory concentration) of nevirapine was 90 nM against a panel of 2923 isolates of HIV-1 that were primarily (93%) clade B clinical isolates from the United States. The 99th percentile EC50 value was 470 nM in this study. The median EC50 value was 63 nM (range 14-302 nM, n=29) against clinical isolates of HIV-1 clades A, B, C, D, F, G, and H, and circulating recombinant forms CRF01_AE, CRF02_AG and CRF12_BF. Nevirapine had no antiviral activity in cell culture against group O HIV-1 isolates (n=3) or HIV-2 isolates (n=3) replicating in cord blood mononuclear cells. Nevirapine in combination with efavirenz exhibited strong antagonistic anti-HIV-1 activity in cell culture and was additive to antagonistic with the protease inhibitor ritonavir or the fusion inhibitor enfuvirtide. Nevirapine exhibited additive to synergistic anti-HIV-1 activity in combination with the protease inhibitors amprenavir, atazanavir, indinavir, lopinavir, nelfinavir, saquinavir and tipranavir, and the NRTIs abacavir, didanosine, emtricitabine, lamivudine, stavudine, tenofovir and zidovudine. The anti-HIV-1 activity of nevirapine was antagonized by the anti-HBV drug adefovir and by the anti-HCV drug ribavirin in cell culture.

Resistance

HIV-1 isolates with reduced susceptibility (100- to 250-fold) to nevirapine emerge in cell culture. Genotypic analysis showed mutations in the HIV-1 RT gene encoding Y181C and/or V106A substitutions depending upon the virus strain and cell line employed. Time to emergence of nevirapine resistance in cell culture was not altered when selection included nevirapine in combination with several other NNRTIs.

Phenotypic and genotypic changes in HIV-1 isolates from treatment-naïve patients receiving either nevirapine (n=24) or nevirapine and ZDV (n=14) were monitored in Phase 1 and 2 trials over 1 to ≥12 weeks. After 1 week of nevirapine monotherapy, isolates from 3/3 patients had decreased susceptibility to nevirapine in cell culture. One or more of the RT mutations resulting in amino acid substitutions K103N, V106A, V108I, Y181C, Y188C and G190A were detected in HIV-1 isolates from some patients as early as 2 weeks after therapy initiation. By week eight of nevirapine monotherapy, 100% of the patients tested (n=24) had HIV-1 isolates with a >100-fold decrease in susceptibility to nevirapine in cell culture compared to baseline, and had one or more of the nevirapine-associated RT resistance substitutions. Nineteen of these patients (80%) had isolates with Y181C substitutions regardless of dose.

Genotypic analysis of isolates from antiretroviral-naïve patients experiencing virologic failure (n=71) receiving nevirapine once daily (n=25) or twice daily (n=46) in combination with lamivudine and stavudine (study 2NN) for 48 weeks showed that isolates from 8/25 and 23/46 patients, respectively, contained one or more of the following NNRTI resistance-associated substitutions: Y181C, K101E, G190A/S, K103N, V106A/M, V108I, Y188C/L, A98G, F227L and M230L.

Cross-resistance

Rapid emergence of HIV-1 strains which are cross-resistant to NNRTIs has been observed in cell culture. Nevirapine-resistant HIV-1 isolates were cross-resistant to the NNRTIs delavirdine and efavirenz. However, nevirapine-resistant isolates were susceptible to the NRTIs ddI and ZDV. Similarly, ZDV-resistant isolates were susceptible to nevirapine in cell culture.

13 NONCLINICAL TOXICOLOGY

13.1 Carcinogenesis, Mutagenesis, Impairment of Fertility

Long-term carcinogenicity studies in mice and rats were carried out with nevirapine. Mice were dosed with 0, 50, 375 or 750 mg/kg/day for two years. Hepatocellular adenomas and carcinomas were increased at all doses in males and at the two high doses in females. In studies in which rats were administered nevirapine at doses of 0, 3.5, 17.5 or 35 mg/kg/day for two years, an increase in hepatocellular adenomas was seen in males at all doses and in females at the high dose. The systemic exposure (based on AUCs) at all doses in the two animal studies was lower than that measured in humans at the 200 mg BID dose. The mechanism of the carcinogenic potential is unknown. However, in genetic toxicology assays, nevirapine showed no evidence of mutagenic or clastogenic activity in a battery of in vitro and in vivo studies. These included microbial assays for gene mutation (Ames: Salmonella strains and E. coli), mammalian cell gene mutation assay (CHO/HGPRT), cytogenetic assays using a Chinese hamster ovary cell line and a mouse bone marrow micronucleus assay following oral administration. Given the lack of genotoxic activity of nevirapine, the relevance to humans of hepatocellular neoplasms in nevirapine-treated mice and rats is not known. In reproductive toxicology studies, evidence of impaired fertility was seen in female rats at doses providing systemic exposure, based on AUC, approximately equivalent to that provided with the recommended clinical dose of VIRAMUNE.

13.2 Animal Toxicology and/or Pharmacology

Animal studies have shown that nevirapine is widely distributed to nearly all tissues and readily crosses the blood-brain barrier.

14 CLINICAL STUDIES

14.1 Clinical Studies in Adults

Trial BI 1090 was a placebo-controlled, double-blind, randomized trial in 2249 HIV-1 infected patients with <200 CD4^+ cells/mm^3 at screening. Initiated in 1995, BI 1090 compared treatment with VIRAMUNE + lamivudine + background therapy versus lamivudine + background therapy in NNRTI-naïve patients. Treatment doses were VIRAMUNE, 200 mg daily for two weeks followed by 200 mg twice daily or placebo, and lamivudine, 150 mg twice daily. Other antiretroviral agents were given at approved doses. Initial background therapy (in addition to lamivudine) was one NRTI in 1309 patients (58%), two or more NRTIs in 771 (34%), and PIs and NRTIs in 169 (8%). The patients (median age 36.5 years, 70% Caucasian, 79% male) had advanced HIV-1 infection, with a median baseline CD4^+ cell count of 96 cells/mm^3 and a baseline HIV-1 RNA of 4.58 log10 copies/mL (38,291 copies/mL). Prior to entering the trial, 45% had previously experienced an AIDS-defining clinical event. Eighty-nine percent had antiretroviral treatment prior to entering the trial. BI 1090 was originally designed as a clinical endpoint study. Prior to unblinding the trial, the primary endpoint was changed to proportion of patients with HIV-1 RNA <50 copies/mL and not previously failed at 48 weeks. Treatment response and outcomes are shown in Table 6.

Table 6 BI 1090 Outcomes Through 48 Weeks
Outcome | VIRAMUNE (N=1121) % |  |  | Placebo (N=1128) %
Responders at 48 weeks: HIV-1 RNA <50 copies/mL | 18.0 |  |  | 1.6
Treatment Failure | 82.0 |  |  | 98.4
Never suppressed viral load |  | 44.6 |  |  | 66.4
Virologic failure after response |  | 7.2 |  |  | 4.3
CDC category C event or death |  | 9.6 |  |  | 11.2
Added antiretroviral therapy^1 while <50 copies/mL |  | 5.0 |  |  | 0.9
Discontinued trial therapy due to AE |  | 7.0 |  |  | 5.9
Discontinued trial <48 weeks^2 |  | 8.5 |  |  | 9.8
^1 including change to open-label nevirapine
^2 includes withdrawal of consent, lost to follow-up, non-compliance with protocol, other administrative reasons

The change from baseline in CD4^+ cell count through one year of therapy was significantly greater for the VIRAMUNE group compared to the placebo group for the overall study population (64 cells/mm^3 vs 22 cells/mm^3, respectively), as well as for patients who entered the trial as treatment naïve or having received only ZDV (85 cells/mm^3 vs 25 cells/mm^3, respectively).

At two years into the study, 16% of subjects on VIRAMUNE had experienced class C CDC events as compared to 21% of subjects on the control arm.

Trial BI 1046 (INCAS) was a double-blind, placebo-controlled, randomized, three-arm trial with 151 HIV-1 infected patients with CD4^+ cell counts of 200-600 cells/mm^3 at baseline. BI 1046 compared treatment with VIRAMUNE+zidovudine+didanosine to VIRAMUNE+zidovudine and zidovudine+didanosine. Treatment doses were VIRAMUNE at 200 mg daily for two weeks followed by 200 mg twice daily or placebo, zidovudine at 200 mg three times daily, and didanosine at 125 or 200 mg twice daily (depending on body weight). The patients had mean baseline HIV-1 RNA of 4.41 log10 copies/mL (25,704 copies/mL) and mean baseline CD4^+ cell count of 376 cells/mm^3. The primary endpoint was the proportion of patients with HIV-1 RNA <400 copies/mL and not previously failed at 48 weeks. The virologic responder rates at 48 weeks were 45% for patients treated with VIRAMUNE+zidovudine+didanosine, 19% for patients treated with zidovudine+didanosine, and 0% for patients treated with VIRAMUNE+zidovudine.

CD4^+ cell counts in the VIRAMUNE+ZDV+ddI group increased above baseline by a mean of 139 cells/mm^3 at one year, significantly greater than the increase of 87 cells/mm^3 in the ZDV+ddI patients. The VIRAMUNE+ZDV group mean decreased by 6 cells/mm^3 below baseline.

14.2 Clinical Studies in Pediatric Patients

The pediatric safety and efficacy of VIRAMUNE was examined in BI Trial 1100.1368, an open-label, randomized clinical study performed in South Africa in which 123 HIV-1 infected treatment-naïve patients between 3 months and 16 years of age received VIRAMUNE oral suspension for 48 weeks. Patients were divided into 4 age groups (3 months to <2 years, 2 to <7 years, 7 to <12 years, and 12 to ≤16 years) and randomized to receive one of two VIRAMUNE doses, determined by 2 different dosing methods [body surface area (150 mg/m^2) and weight-based dosing (4 or 7 mg/kg)] in combination with zidovudine and lamivudine [see Adverse Reactions (6.2), Use in Specific Populations (8.4), and Clinical Pharmacology (12.3)]. The total daily dose of VIRAMUNE did not exceed 400 mg in either regimen. There were 66 patients in the body surface area (BSA) dosing group and 57 patients in the weight-based (BW) dosing group.

Baseline demographics included: 49% male; 81% Black and 19% Caucasian; 4% had previous exposure to ARVs. Patients had a median baseline HIV-1 RNA of 5.45 log10 copies/mL and a median baseline CD4^+ cell count of 527 cells/mm^3 (range 37-2279). One hundred and five (85%) completed the 48-week period while 18 (15%) discontinued prematurely. Of the patients who discontinued prematurely, 9 (7%) discontinued due to adverse reactions and 3 (2%) discontinued due to virologic failure. Overall the proportion of patients who achieved and maintained an HIV-1 RNA <400 copies/mL at 48 weeks was 47% (58/123).

For dose recommendations for pediatric patients [see Dosage and Administration (2.2)].

16 HOW SUPPLIED/STORAGE AND HANDLING

VIRAMUNE tablets, 200 mg, are white, oval, biconvex tablets, 9.3 mm x 19.1 mm. One side is embossed with "54 193", with a single bisect separating the "54" and "193". The opposite side has a single bisect.

Dispense in tight container as defined in the USP/NF.

VIRAMUNE oral suspension is a white to off-white preserved suspension containing 50 mg nevirapine (as nevirapine hemihydrate) in each 5 mL.

They are supplied by State of Florida DOH Central Pharmacy as follows:

NDC | Strength | Quantity/Form | Color | Source Prod. Code
53808-0808-1 | 200 mg | 30 Tablets in a Blister Pack | WHITE | 0597-0046

Storage

Store at 25°C (77°F); excursions permitted to 15°–30°C (59°–86°F) [see USP Controlled Room Temperature]. Store in a safe place out of the reach of children.

This product was Manufactured By:
Boehringer Ingelheim Pharmaceuticals, Inc.
900 Ridgebury Road
P.O. Box 368
Ridgefield, CT 06877

And Repackaged By:

State of Florida DOH Central Pharmacy
104-2 Hamilton Park Drive
Tallahassee, FL 32304
United States

17 PATIENT COUNSELING INFORMATION

See MEDICATION GUIDE

The Medication Guide provides written information for the patient, and should be dispensed with each new prescription and refill.

A Medication Guide is supplied as a tear-off following the full prescribing information.

ATTENTION PHARMACISTS: Detach "Medication Guide" and dispense with the product.

17.1 Hepatotoxicity and Skin Reactions

Patients should be informed of the possibility of severe liver disease or skin reactions associated with VIRAMUNE that may result in death. Patients developing signs or symptoms of liver disease or severe skin reactions should be instructed to discontinue VIRAMUNE and seek medical attention immediately, including performance of laboratory monitoring. Symptoms of liver disease include fatigue, malaise, anorexia, nausea, jaundice, acholic stools, liver tenderness or hepatomegaly. Symptoms of severe skin or hypersensitivity reactions include rash accompanied by fever, general malaise, fatigue, muscle or joint aches, blisters, oral lesions, conjunctivitis, facial edema and/or hepatitis.

Intensive clinical and laboratory monitoring, including liver enzymes, is essential during the first 18 weeks of therapy with VIRAMUNE to detect potentially life-threatening hepatotoxicity and skin reactions. However, liver disease can occur after this period; therefore, monitoring should continue at frequent intervals throughout VIRAMUNE treatment. Extra vigilance is warranted during the first 6 weeks of therapy, which is the period of greatest risk of hepatic events and skin reactions. Patients with signs and symptoms of hepatitis should discontinue VIRAMUNE and seek medical evaluation immediately. If VIRAMUNE is discontinued due to hepatotoxicity, do not restart it. Patients, particularly women, with increased CD4^+ cell count at initiation of VIRAMUNE therapy (>250 cells/mm^3 in women and >400 cells/mm^3 in men) are at substantially higher risk for development of symptomatic hepatic events, often associated with rash. Patients should be advised that co-infection with hepatitis B or C and/or increased transaminases at the start of therapy with VIRAMUNE are associated with a greater risk of later symptomatic events (6 weeks or more after starting VIRAMUNE) and asymptomatic increases in AST or ALT [see Boxed Warning and Warnings and Precautions (5.1)].

The majority of rashes associated with VIRAMUNE occur within the first 6 weeks of initiation of therapy. Patients should be instructed that if any rash occurs during the two-week lead-in period, the VIRAMUNE dose should not be escalated until the rash resolves. The total duration of the once-daily lead-in dosing period should not exceed 28 days, at which point an alternative regimen may need to be started. Any patient experiencing a rash should have their liver enzymes (AST, ALT) evaluated immediately. Patients with severe rash or hypersensitivity reactions should discontinue VIRAMUNE immediately and consult a physician. VIRAMUNE should not be restarted following severe skin rash or hypersensitivity reaction. Women tend to be at higher risk for development of VIRAMUNE-associated rash [see Boxed Warning and Warnings and Precautions (5.2)].

17.2 Administration

Patients should be informed to take VIRAMUNE every day as prescribed. Patients should not alter the dose without consulting their doctor. If a dose is missed, patients should take the next dose as soon as possible. However, if a dose is skipped, the patient should not double the next dose. Patients should be advised to report to their doctor the use of any other medications.

Patients should be informed that VIRAMUNE therapy has not been shown to reduce the risk of transmission of HIV-1 to others through sexual contact or blood contamination. The long-term effects of VIRAMUNE are unknown at this time.

VIRAMUNE is not a cure for HIV-1 infection; patients may continue to experience illnesses associated with advanced HIV-1 infection, including opportunistic infections. Patients should be advised to remain under the care of a physician when using VIRAMUNE.

17.3 Drug Interactions

VIRAMUNE may interact with some drugs; therefore, patients should be advised to report to their doctor the use of any other prescription, non-prescription medication or herbal products, particularly St. John's wort [see Warnings and Precautions (5.4) and Drug Interactions (7)].

17.4 Contraceptives

Hormonal methods of birth control, other than depomedroxy-progesterone acetate (DMPA), should not be used as the sole method of contraception in women taking VIRAMUNE, since VIRAMUNE may lower the plasma levels of these medications. Additionally, when oral contraceptives are used for hormonal regulation during VIRAMUNE therapy, the therapeutic effect of the hormonal therapy should be monitored [see Drug Interactions (7)].

17.5 Methadone

VIRAMUNE may decrease plasma concentrations of methadone by increasing its hepatic metabolism. Narcotic withdrawal syndrome has been reported in patients treated with VIRAMUNE and methadone concomitantly. Methadone-maintained patients beginning nevirapine therapy should be monitored for evidence of withdrawal and methadone dose should be adjusted accordingly [see Drug Interactions (7)].

17.6 Fat Redistribution

Patients should be informed that redistribution or accumulation of body fat may occur in patients receiving antiretroviral therapy and that the cause and long-term health effects of these conditions are not known at this time [see Warnings and Precautions (5.6)].

MEDICATION GUIDE

VIRAMUNE® (VIH-rah-mune)
(nevirapine)
Tablets
VIRAMUNE® (VIH-rah-mune)
(nevirapine)
Oral Suspension

Read this Medication Guide before you start taking VIRAMUNE and each time you get a refill. There may be new information. This information does not take the place of talking to your doctor about your medical condition or treatment.

What is the most important information I should know about VIRAMUNE?

VIRAMUNE can cause serious side effects. These include severe liver and skin problems which can cause death. The risk of these problems is greatest during the first 18 weeks of treatment, but these problems can also happen at any time during treatment.

Severe liver problems: Anyone who takes VIRAMUNE may get severe liver problems. In some cases, these liver problems can lead to liver failure and the need for a liver transplant, or death. You may get a rash if you have liver problems. People with higher risk of these problems include women or anyone with higher CD4^+ cell counts when they begin VIRAMUNE treatment. Women with CD4^+ cell counts higher than 250 cells/mm^3 at the start of treatment have the greatest risk for liver damage.

If you are a woman with CD4^+ cell >250 cells/mm^3 or a man with CD4^+ cell >400 cells/mm^3, you and your doctor will decide if VIRAMUNE is right for you.

People who have abnormal liver test results and people with hepatitis B or C have a greater chance of getting liver problems and further increases in liver test results during treatment.

If you get any of the following symptoms of liver problems, stop taking VIRAMUNE and call your doctor right away:

- fever
- "flu-like" symptoms or you do not feel well
- dark (tea colored) urine
- tiredness
- light-colored bowel movements (stools)
- nausea (feeling sick to your stomach)
- pain or tenderness on your right side below your ribs
- loss of appetite
- yellowing of your skin or whites of your eyes

Your doctor should see you and do blood tests often to check your liver function during the first 18 weeks of treatment with VIRAMUNE. You should continue to have your liver checked regularly during your treatment with VIRAMUNE. It is important for you to keep all of your doctor appointments.

Severe rash and skin reactions: Skin rash is the most common side effect of VIRAMUNE. Most rashes happen in the first 6 weeks of taking VIRAMUNE. Rashes and skin reactions may be severe, life-threatening, and in some people, may lead to death. If you get a rash with any of the following symptoms, stop using VIRAMUNE and call your doctor right away:

- "flu-like" symptoms or you do not feel well
- blisters
- fever
- mouth sores
- muscle or joint aches
- swelling of your face
- red or inflamed eyes, like "pink eye" (conjunctivitis)
- tiredness
- swollen glands (enlarged lymph nodes)
- liver problems (see symptoms of liver problems above)

If your doctor tells you to stop treatment with VIRAMUNE because you have had the serious liver or skin problems described above, you should never take VIRAMUNE again.

These are not all the side effects of VIRAMUNE. See the section "What are the possible side effects of VIRAMUNE?" for more information.

What is VIRAMUNE?
VIRAMUNE is a medicine used to treat Human Immunodeficiency Virus (HIV), the virus that causes AIDS (Acquired Immune Deficiency Syndrome).

VIRAMUNE is a type of anti-HIV medicine called a "non-nucleoside reverse transcriptase inhibitor" (NNRTI). VIRAMUNE works by lowering the amount of HIV in your blood ("viral load"). You must take VIRAMUNE with other anti-HIV medicines. When you take VIRAMUNE with other anti-HIV medicines, VIRAMUNE can lower your viral load and increase the number of CD4^+ cells ("T cells"). CD4^+ cells are a type of immune helper cell in the blood. VIRAMUNE may not have these effects in every person.

VIRAMUNE does not cure HIV or AIDS, and it is not known if it will help you live longer with HIV. People taking VIRAMUNE may still get infections common in people with HIV (opportunistic infections). It is very important that you stay under the care of your doctor.

Who should not take VIRAMUNE?
Tell your doctor if you have or have had liver problems. Your doctor may tell you not to take VIRAMUNE if you have certain liver problems.

What should I tell my doctor before taking VIRAMUNE?

Before you take VIRAMUNE, tell your doctor if you:

- have or have had hepatitis (inflammation of your liver) or problems with your liver. See "What is the most important information I should know about VIRAMUNE?" and "Who should not take VIRAMUNE?"
- receive dialysis
- have skin problems, such as a rash
- are pregnant or plan to become pregnant. It is not known if VIRAMUNE will harm your unborn baby.
  Pregnancy Registry: There is a pregnancy registry for women who take antiviral medicines during pregnancy. The purpose of the registry is to collect information about the health of you and your baby. Talk to your doctor about how you can take part in this registry.
- are breast-feeding or plan to breast-feed. VIRAMUNE can pass into your breast milk and may harm your baby. It is also recommended that HIV-positive women should not breast-feed their babies. Do not breast-feed during treatment with VIRAMUNE. Talk to your doctor about the best way to feed your baby.

Tell your doctor and pharmacist about all the medicines you take, including prescription and non-prescription medicines, vitamins and herbal supplements. VIRAMUNE may affect the way other medicines work, and other medicines may affect how VIRAMUNE works. Especially tell your doctor if you take:

- St. John’s Wort. You should not take products containing St. John’s Wort during treatment with VIRAMUNE because it can lower the amount of VIRAMUNE in your body.
- efavirenz (Sustiva®, Atripla®). You should not take efavirenz during treatment with VIRAMUNE. You may have an increased chance of side effects if this is taken together with VIRAMUNE.
- atazanavir (Reyataz®). You should not take atazanavir during treatment with VIRAMUNE.
- itraconazole (Sporanox®). You should not take itraconazole during treatment with VIRAMUNE.
- ketoconazole (Nizoral®). You should not take ketoconazole during treatment with VIRAMUNE.
- rifampin (Rifadin®, Rifamate®, Rifater®). You should not take rifampin during treatment with VIRAMUNE.
- Birth control pills. Birth control pills taken by mouth (oral contraceptives) and other hormone types of birth control may not work to prevent pregnancy if you use them during VIRAMUNE treatment. Talk with your doctor about other types of birth control that you can use to prevent pregnancy during treatment with VIRAMUNE.

Also tell your doctor if you are taking the following drugs:

- clarithromycin (Biaxin)
- fluconazole (Diflucan)
- methadone
- rifabutin (Mycobutin)

Know the medicines you take. Keep a list of them to show your doctor or pharmacist when you get a new medicine.

How should I take VIRAMUNE?

- Take VIRAMUNE exactly as your doctor tells you to take it.
- The dose of VIRAMUNE for children is based on their size and thus may not be the same as in adults.
- You may take VIRAMUNE with or without food.
- If you or your child takes VIRAMUNE suspension (liquid), shake it gently before use. Use an oral dosing syringe or dosing cup to measure the right dose. The oral dosing syringe and dosing cup are not provided with VIRAMUNE Suspension.
- After drinking the medicine, fill the dosing cup with water and drink it to make sure you get all the medicine. If the dose is less than 1 teaspoon (5 mL), use the syringe instead of the dosing cup.
- Do not change your dose unless your doctor tells you to.
- Your doctor should start you with one dose each day to lower your chance of getting a serious rash. It is important that you only take one dose of VIRAMUNE each day for the first 14 days.
- Call your doctor right away if you get a skin rash during the first 14 days of VIRAMUNE treatment and do not increase your dose to 2 times a day.
- You should never take your starting dose (200 mg one time each day) for longer than 28 days. If after 28 days you are still receiving this starting dose because you have a rash, you and your doctor should discuss replacing VIRAMUNE with another HIV medicine. Never increase your dose to 2 times a day if you have a rash.
- Do not miss a dose of VIRAMUNE, because this could make HIV harder to treat. If you miss a dose of VIRAMUNE, take the missed dose as soon as you remember. If it is almost time for your next dose, do not take the missed dose, just take the next dose at your regular time.
- If you stop taking VIRAMUNE for more than 7 days, ask your doctor how much to take before you start taking it again. You may need to start with one time each day dosing again.
- If you take too much VIRAMUNE, call your local poison control center or emergency room right away.

What are the possible side effects of VIRAMUNE?
VIRAMUNE may cause serious side effects.

- See "What is the most important information I should know about VIRAMUNE?"
- Other common side effects of VIRAMUNE include nausea, fatigue, fever, headache, vomiting, diarrhea, abdominal pain, and muscle pain.
- Changes in your immune system (Immune Reconstitution Syndrome) can happen when you start taking HIV medicines. Your immune system may get stronger and begin to fight infections that have been hidden in your body for a long time. Tell your doctor if you start having new symptoms after starting your HIV medicine.
- Changes in body fat can happen in some people who take antiretroviral therapy. These changes may include increased amount of fat in the upper back and neck ("buffalo hump"), breast, and around the middle of your body (trunk). Loss of fat from your legs, arms, and face can also happen. The cause and long-term health effects of these problems are not known at this time.

Tell your doctor if you have any side effect that bothers you or that does not go away.

These are not all the possible side effects of VIRAMUNE. For more information, ask your doctor or pharmacist.

Call your doctor for medical advice about side effects. You may report side effects to FDA at 1-800-FDA-1088.

How should I store VIRAMUNE?

- Store VIRAMUNE at 59° to 86°F (15° to 30°C).
- Throw away VIRAMUNE that is no longer needed or out-of-date.

Keep VIRAMUNE and all medicines out of the reach of children.

General information about VIRAMUNE
Medicines are sometimes prescribed for purposes other than those listed in a Medication Guide. Do not use VIRAMUNE for a condition for which it was not prescribed. Do not give VIRAMUNE to other people, even if they have the same condition you have. It may harm them.

This Medication Guide summarizes the most important information about VIRAMUNE. If you would like more information, talk with your doctor. You can ask your pharmacist or doctor for information about VIRAMUNE that is written for health professionals.

For more information, call Boehringer Ingelheim Pharmaceuticals, Inc., at 1-800-542-6257, or (TTY) 1-800-459-9906.

What are the ingredients in VIRAMUNE?
Active Ingredient: nevirapine
Inactive ingredients:
Viramune Tablets: microcrystalline cellulose, lactose monohydrate, povidone, sodium starch glycolate, colloidal silicon dioxide, and magnesium stearate
Viramune Oral Suspension: carbomer 934P, methylparaben, propylparaben, sorbitol, sucrose, polysorbate 80, sodium hydroxide, and purified water

This Medication Guide has been approved by the US Food and Drug Administration

Atripla, Reyataz, and Sustiva are trademarks of Bristol Myers Squibb. Biaxin is a trademark of Abbott Laboratories. Diflucan is a trademark of Pfizer, Inc. Mycobutin is a trademark of Pharmacia & Upjohn Company. Nizoral and Sporanox are trademarks of Janssen Pharmaceutica. Rifadin, Rifamate, and Rifater are trademarks of Aventis Pharmaceuticals, Inc.

PACKAGE LABEL

Viramune

200 mg

NDC 53808-0808-1